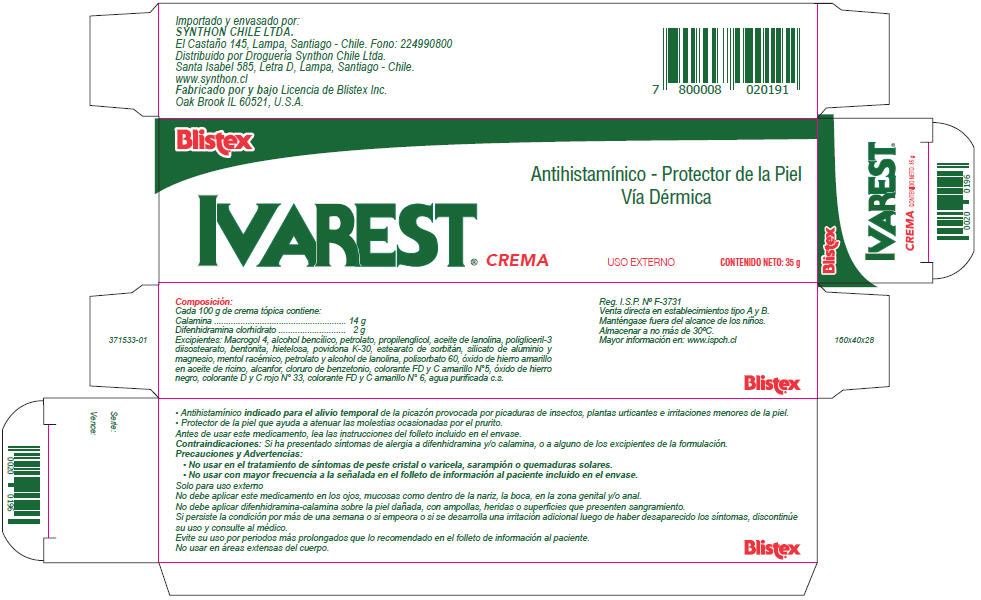 DRUG LABEL: Blistex Ivarest
NDC: 10157-9014 | Form: CREAM
Manufacturer: Blistex Inc.
Category: otc | Type: HUMAN OTC DRUG LABEL
Date: 20170512

ACTIVE INGREDIENTS: ZINC OXIDE 14 g/100 g; DIPHENHYDRAMINE HYDROCHLORIDE 2 g/100 g
INACTIVE INGREDIENTS: WATER; POLYETHYLENE GLYCOL 200; BENZYL ALCOHOL; PETROLATUM; PROPYLENE GLYCOL; LANOLIN OIL; POLYGLYCERYL-3 DIISOSTEARATE; BENTONITE; HYDROXYETHYL ETHYLCELLULOSE; POVIDONE, UNSPECIFIED; SORBITAN MONOSTEARATE; MAGNESIUM ALUMINUM SILICATE; MENTHOL, UNSPECIFIED FORM; LANOLIN ALCOHOLS; POLYSORBATE 60; FERRIC OXIDE YELLOW; CASTOR OIL; CAMPHOR (SYNTHETIC); BENZETHONIUM CHLORIDE; FD&C YELLOW NO. 5; FERROSOFERRIC OXIDE; D&C RED NO. 33; FD&C YELLOW NO. 6

Blistex Ivarest® Crema

PRINCIPAL DISPLAY PANEL - 35 g Tube Carton

Blistex

IVAREST®